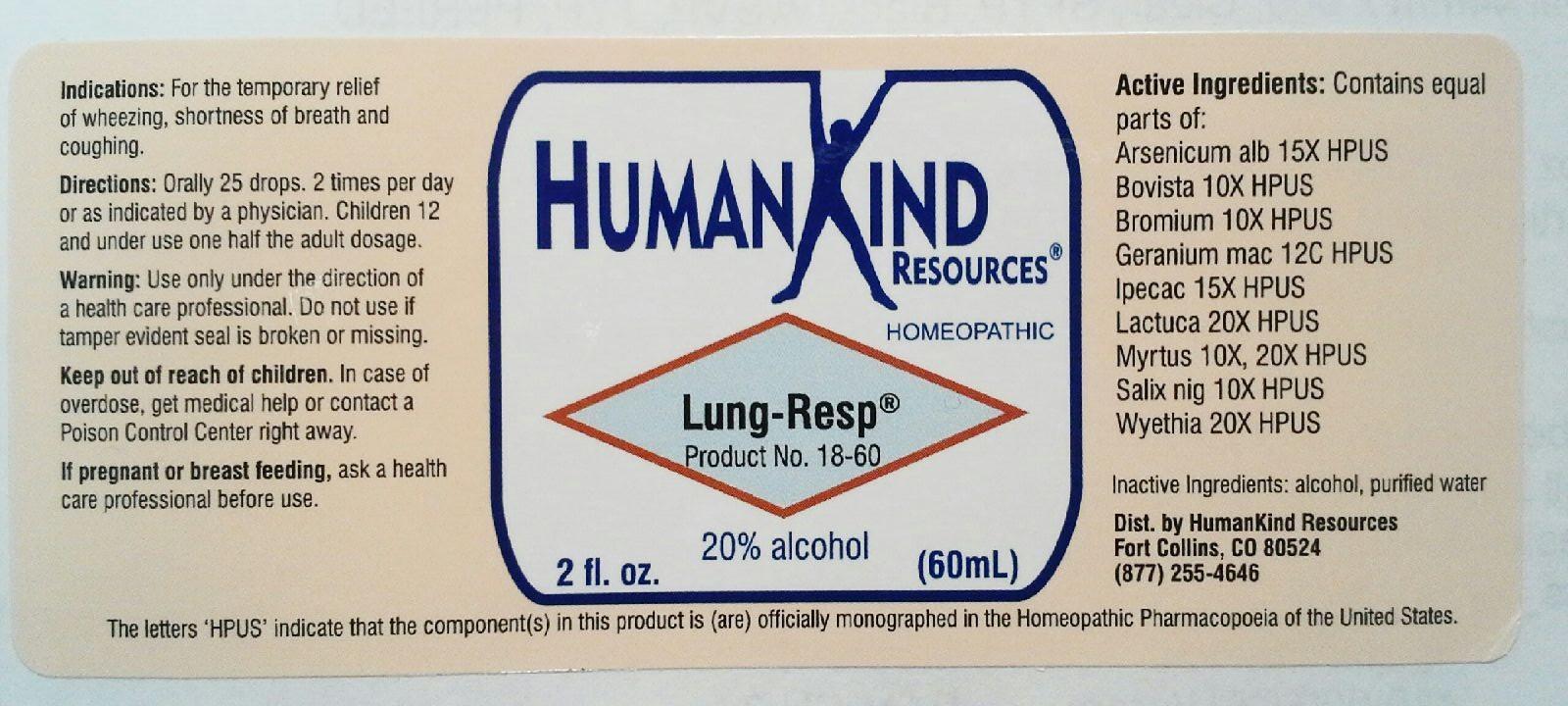 DRUG LABEL: Lung-Resp
NDC: 64616-096 | Form: LIQUID
Manufacturer: Vitality Works, Inc
Category: homeopathic | Type: HUMAN OTC DRUG LABEL
Date: 20251217

ACTIVE INGREDIENTS: ARSENIC TRIOXIDE 15 [hp_X]/1 mL; LYCOPERDON UTRIFORME FRUITING BODY 10 [hp_X]/1 mL; BROMINE 10 [hp_X]/1 mL; GERANIUM MACULATUM ROOT 12 [hp_C]/1 mL; IPECAC 15 [hp_X]/1 mL; LACTUCA VIROSA 20 [hp_X]/1 mL; MYRTUS COMMUNIS TOP 20 [hp_X]/1 mL; SALIX NIGRA BARK 10 [hp_X]/1 mL; WYETHIA HELENIOIDES ROOT 20 [hp_X]/1 mL
INACTIVE INGREDIENTS: ALCOHOL; WATER

Lung-Resp

Lung-Resp

Arsenicum Album 15X Lactuca Virosa 20X

Bovista 10X Myrtus Communis 10X, 20X

Bromium 10X Salix Nigra 10X

Geranimun Maculatum 12C Wyethia Helenioides 20X

Ipecacuanha 15X

Lung-Resp

Alcohol, Purified Water

Lung-Resp

Use only under the direction of a health care professional. Do not use if tamper evident seal is broken or missing.

Lung-Resp

Keep out of reach of children. In case overdose get medical help or contact a Poison Control Center right away.

Lung-Resp

For the temporary relief of wheezing, shortness of breath and coughing.

Lung-Resp

Orally 25 drops, 2 times per day or as indicated by a physician. Children 12 and under use one half the adult dose.

Lung-Resp

Temporarly eases wheezing, shortness of breath and coughing.